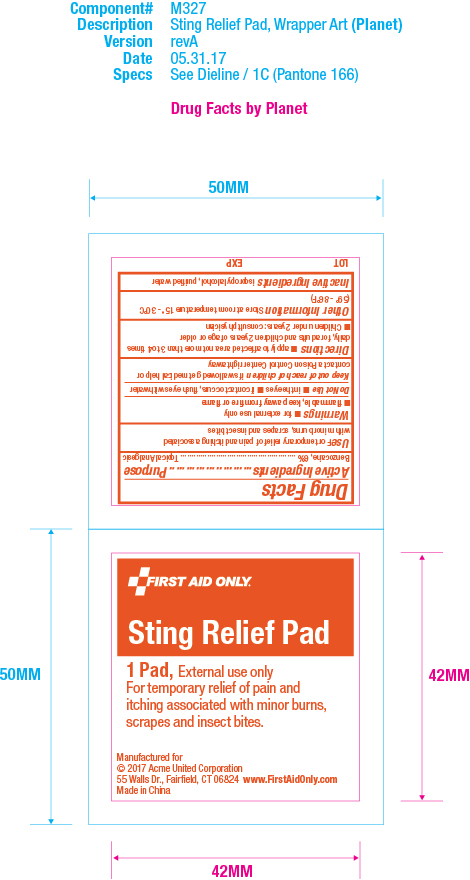 DRUG LABEL: First Aid Only Sting Relief Pad
NDC: 0924-5201 | Form: PATCH
Manufacturer: Acme United Corporation
Category: otc | Type: HUMAN OTC DRUG LABEL
Date: 20241119

ACTIVE INGREDIENTS: BENZOCAINE 6 g/100 g
INACTIVE INGREDIENTS: ISOPROPYL ALCOHOL; WATER

First Aid Only Sting Relief Pad

Active Ingredients

Active Ingredients Benzocaine, 6%

Purpose

Topical Analgesic

Use

Use For temporary relief of pain and itching associated with minor burns, scapes and insect bites

Warnings

Warnings •for external use only •flammable, keep away from fire or flame

Do Not Use •in the eyes •if contact occurs, flush eyes with water

Keep out of reach of children if swallowed get medical help or contact a Poison Control Center right away

Directions

Directions •apply to affected area not more than 3 to 4 times daily, for adults and children 2 years of age or older

•Children under 2 years: consult physician

Other Information

Other Information Store at room temperature 15° - 30°C (59° - 86°F)

Inactive Ingredients

Inactive Ingredients isopropyl alcohol, purified water